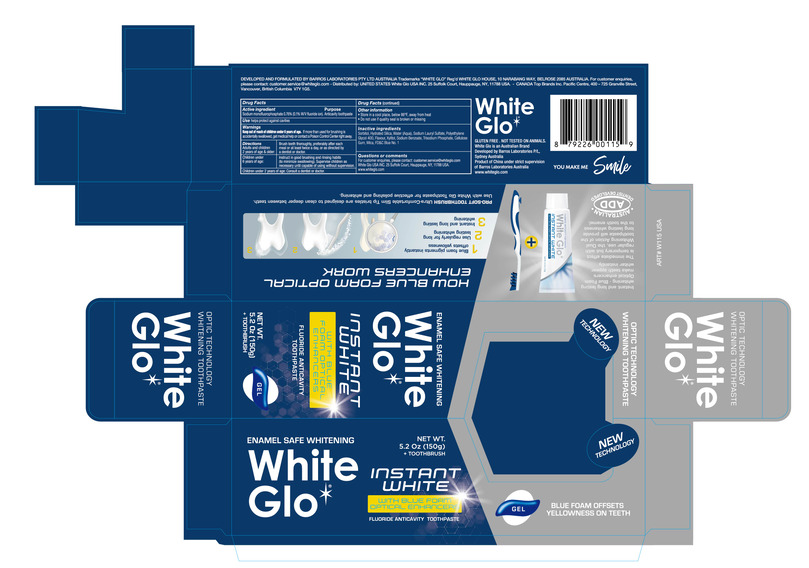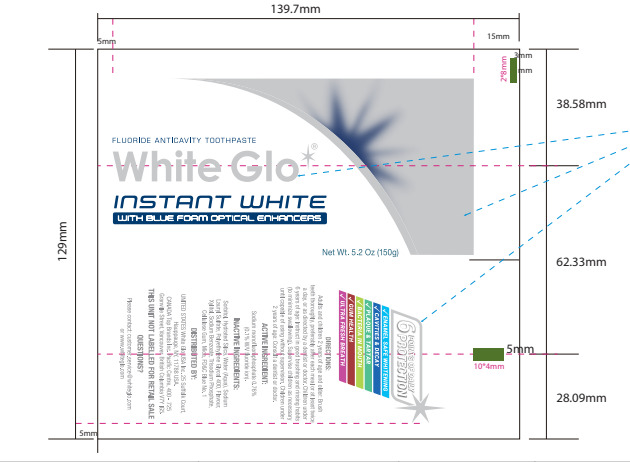 DRUG LABEL: Instant Whitening
NDC: 82168-002 | Form: PASTE, DENTIFRICE
Manufacturer: Guangzhou City Caiye Cosmetics CO., Ltd
Category: otc | Type: HUMAN OTC DRUG LABEL
Date: 20241129

ACTIVE INGREDIENTS: SODIUM MONOFLUOROPHOSPHATE 0.76 g/100 g
INACTIVE INGREDIENTS: SORBITOL; SILICA; AQUA; SODIUM LAURYL SULFATE; POLYETHYLENE GLYCOL 400; XYLITOL; SODIUM BENZOATE; CELLULOSE GUM; MICA

82168-002

Active Ingredient(s)

Sodium monofluorophosphate 0.76%

Purpose

Anticavity tothpaste

Use

Use helps protect against cavities

Warnings

Keep out of reach of children under 6years of age. If more than used for brushingis
accidentally swallowed, getmedical helpor contact a PoisonControlCenter right away.

Do not use on open skin wounds

WHEN USING

Please keep away from your eyes when using this product

STOP USE

If in contact with the eyes, rinse thoroughly with water.

keep out of reach of children under 6 years of age

Directions

Adults and children 2 years of age & older: Brush teeth thoroughly, preferably after each meal or at least twice a day, or as directed by
a dentist or doctor.
Children under 6 years of age: Instruct in good brushing and rinsing habits (to minimize swallowing). Supervise children as
necessary until capable of using without supervision.
Children under 2 years of age: Consult a dentist or doctor.

Other information

●Store in a cool place, below 86°F, away from heat
●Do not use if quality seal is broken or missing

Inactive ingredients

Sorbito, Hydrated Slica, Water (Aqua), Sodium Laury Sulfate, Polyethylene
Glycol 400, Flavour, Xyitol, Sodium Benzoate, Trisodium Phosphate, Clulose
Gum, Mica, FD&C Blue No.1